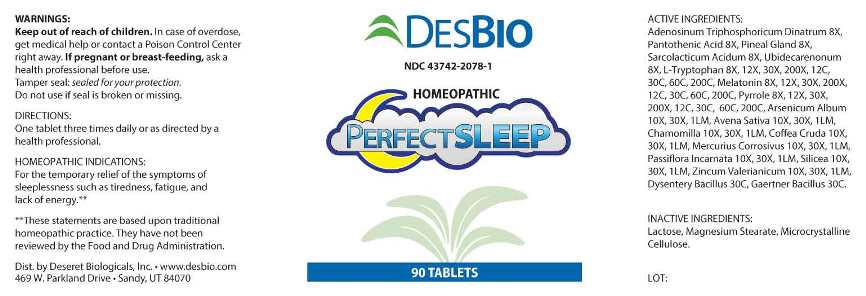 DRUG LABEL: Perfect Sleep
NDC: 43742-2078 | Form: TABLET
Manufacturer: Deseret Biologicals, Inc.
Category: homeopathic | Type: HUMAN OTC DRUG LABEL
Date: 20230220

ACTIVE INGREDIENTS: ADENOSINE TRIPHOSPHATE DISODIUM 8 [hp_X]/1 1; PANTOTHENIC ACID 8 [hp_X]/1 1; SUS SCROFA PINEAL GLAND 8 [hp_X]/1 1; LACTIC ACID, L- 8 [hp_X]/1 1; UBIDECARENONE 8 [hp_X]/1 1; TRYPTOPHAN 8 [hp_X]/1 1; MELATONIN 8 [hp_X]/1 1; PYRROLE 8 [hp_X]/1 1; ARSENIC TRIOXIDE 10 [hp_X]/1 1; AVENA SATIVA FLOWERING TOP 10 [hp_X]/1 1; MATRICARIA CHAMOMILLA WHOLE 10 [hp_X]/1 1; ARABICA COFFEE BEAN 10 [hp_X]/1 1; MERCURIC CHLORIDE 10 [hp_X]/1 1; PASSIFLORA INCARNATA FLOWERING TOP 10 [hp_X]/1 1; SILICON DIOXIDE 10 [hp_X]/1 1; ZINC VALERATE DIHYDRATE 10 [hp_X]/1 1; SHIGELLA DYSENTERIAE 30 [hp_C]/1 1; SALMONELLA ENTERICA SUBSP. ENTERICA SEROVAR ENTERITIDIS 30 [hp_C]/1 1
INACTIVE INGREDIENTS: LACTOSE MONOHYDRATE; MAGNESIUM STEARATE; CELLULOSE, MICROCRYSTALLINE

DRUG FACTS:

ACTIVE INGREDIENTS:

Adenosinum Triphosphoricum Dinatrum 8X, Pantothenic Acid 8X, Pineal Gland (Suis) 8X, Sarcolacticum Acidum 8X, Ubidecarenonum 8X, L-Tryptophan 8X, 12X, 30X, 200X, 12C, 30C, 60C, 200C, Melatonin 8X, 12X, 30X, 200X, 12C, 30C, 60C, 200C, Pyrrole 8X, 12X, 30X, 200X, 12C, 30C, 60C, 200C, Arsenicum Album 10X, 30X, 1LM, Avena Sativa 10X, 30X, 1LM, Chamomilla 10X, 30X, 1LM, Coffea Cruda 10X, 30X, 1LM, Mercurius Corrosivus 10X, 30X, 1LM, Passiflora Incarnata 10X, 30X, 1LM, Silicea 10X, 30X, 1LM, Zincum Valerianicum 10X, 30X, 1LM, Dysentery Bacillus 30C, Gaertner Bacillus (Bach) 30C.

PURPOSE:

For the temporary relief of the symptoms of sleeplessness such as tiredness, fatigue, and lack of energy.**

**These statements are based upon traditional homeopathic principles. They have not been reviewed by the Food and Drug Administration.

WARNINGS:

Keep out of reach of children. In case of overdose, get medical help or contact a Poison Control Center right away.

If pregnant or breast-feeding, ask a health professional before use.

Tamper seal: sealed for your protection.

Do not use if seal is broken or missing.

Keep out of reach of children. In case of overdose, get medical help or contact a Poison Control Center right away.

DIRECTIONS:

One tablet three times daily or as directed by a health professional.

INDICATIONS:

For the temporary relief of the symptoms of sleeplessness such as tiredness, fatigue, and lack of energy.**

**These statements are based upon traditional homeopathic principles. They have not been reviewed by the Food and Drug Administration.

INACTIVE INGREDIENTS:

Lactose, Magnesium Stearate, Microcrystalline Cellulose.

QUESTIONS:

Dist. by Deseret Biologicals, Inc. • www.desbio.com

469 W. Parkland Drive, • Sandy, UT 84070

PACKAGE LABEL DISPLAY:

DESBIO

NDC 43742-2078-1

HOMEOPATHIC

PERFECTSLEEP

90 TABLETS